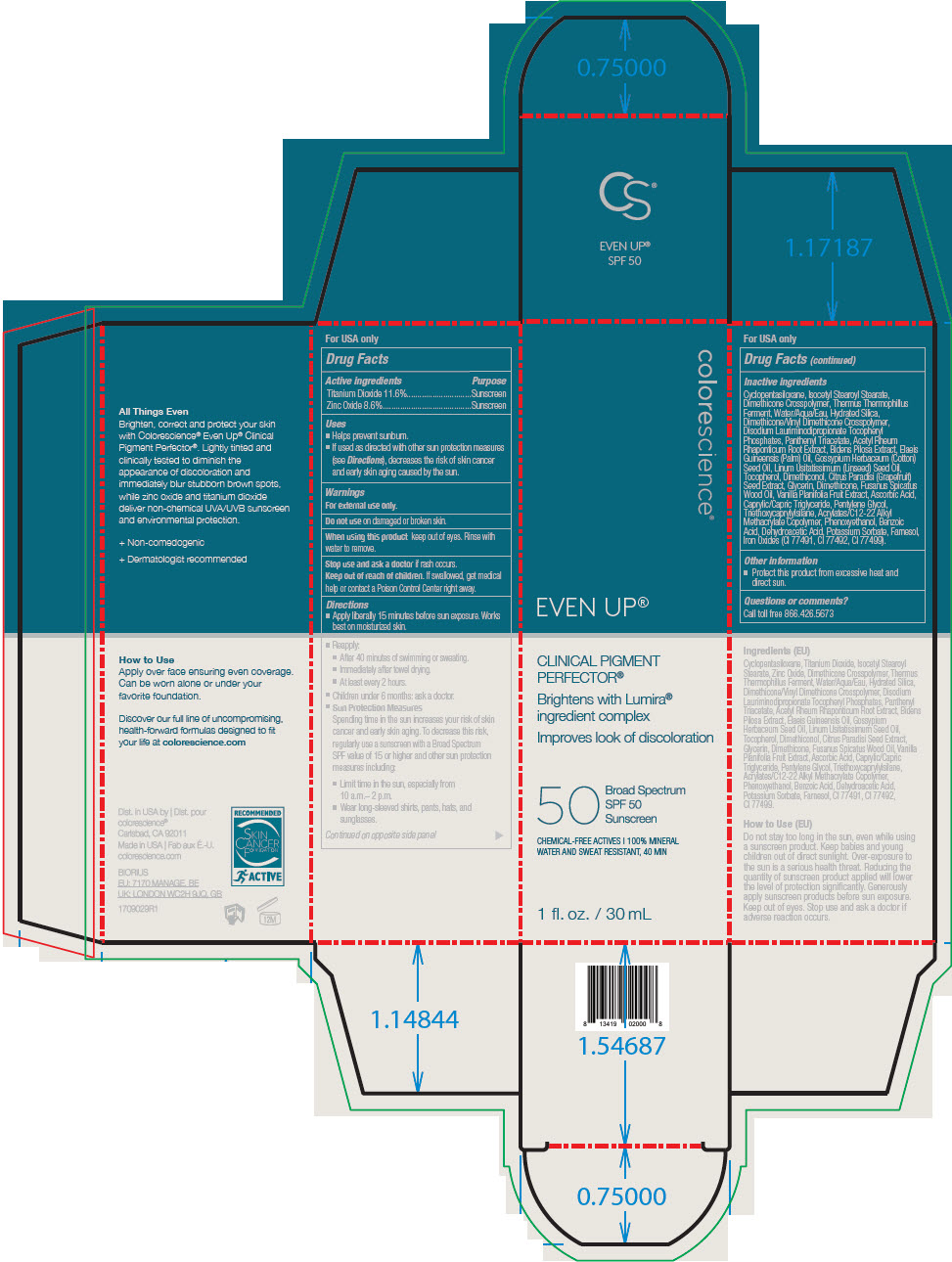 DRUG LABEL: Even Up Sunscreen SPF 50
NDC: 68078-003 | Form: LIQUID
Manufacturer: Colorescience
Category: otc | Type: HUMAN OTC DRUG LABEL
Date: 20241217

ACTIVE INGREDIENTS: Titanium Dioxide 116 mg/1 mL; Zinc Oxide 86 mg/1 mL
INACTIVE INGREDIENTS: Cyclomethicone 5; Isocetyl Stearoyl Stearate; Dimethicone/Vinyl Dimethicone Crosspolymer (Soft Particle); Thermus Thermophilus Lysate; Water; Panthenol Triacetate, (+)-; Disodium Lauriminodipropionate Tocopheryl Phosphates; Glycerin; Dimethicone; Palm Oil; Cottonseed Oil; Citrus Paradisi Seed; Triethoxycaprylylsilane; Linseed Oil; Santalum Spicatum Oil; Ascorbic Acid; Pentylene Glycol; Medium-Chain Triglycerides; Phenoxyethanol; VANILLA BEAN; Potassium Sorbate; Benzoic Acid; Dehydroacetic Acid; Tocopherol; DIMETHICONE CROSSPOLYMER (450000 MPA.S AT 12% IN CYCLOPENTASILOXANE); FERRIC OXIDE YELLOW; FERRIC OXIDE RED; FERROSOFERRIC OXIDE; BUTYL ACRYLATE/C16-C20 ALKYL METHACRYLATE/METHACRYLIC ACID/METHYL METHACRYLATE COPOLYMER; DIMETHICONOL (100000 CST); Hydrated Silica

Even Up® Sunscreen SPF 50

Drug Facts

ACTIVE INGREDIENT

Active ingredients | Purpose
Titanium Dioxide 11.6% | Sunscreen
Zinc Oxide 8.6% | Sunscreen

Uses

- Helps prevent sunburn.
- If used as directed with other sun protection measures (see Directions), decreases the risk of skin cancer and early skin aging caused by the sun.

Warnings

For external use only.

Do not use on damaged or broken skin.

When using this product keep out of eyes. Rinse with water to remove.

Stop use and ask a doctor if rash occurs.

Keep out of reach of children. If swallowed, get medical help or contact a Poison Control Center right away.

Directions

- Apply liberally 15 minutes before sun exposure. Works best on moisturized skin.
- Reapply:
  - After 40 minutes of swimming or sweating.
  - Immediately after towel drying.
  - At least every 2 hours.
- Children under 6 months: ask a doctor.
- Sun Protection Measures
  Spending time in the sun increases your risk of skin cancer and early skin aging. To decrease this risk, regularly use a sunscreen with a Broad Spectrum SPF value of 15 or higher and other sun protection measures including:
  - Limit time in the sun, especially from 10 a.m.– 2 p.m.
  - Wear long-sleeved shirts, pants, hats, and sunglasses.

Inactive ingredients

Cyclopentasiloxane, Isocetyl Stearoyl Stearate, Dimethicone Crosspolymer, Thermus Thermophillus Ferment, Water/Aqua/Eau, Hydrated Silica, Dimethicone/Vinyl Dimethicone Crosspolymer, Disodium Lauriminodipropionate Tocopheryl Phosphates, Panthenyl Triacetate, Acetyl Rheum Rhaponticum Root Extract, Bidens Pilosa Extract, Elaeis Guineensis (Palm) Oil, Gossypium Herbaceum (Cotton) Seed Oil, Linum Usitatissimum (Linseed) Seed Oil, Tocopherol, Dimethiconol, Citrus Paradisi (Grapefruit) Seed Extract, Glycerin, Dimethicone, Fusanus Spicatus Wood Oil, Vanilla Planifolia Fruit Extract, Ascorbic Acid, Caprylic/Capric Triglyceride, Pentylene Glycol, Triethoxycaprylylsilane, Acrylates/C12-22 Alkyl Methacrylate Copolymer, Phenoxyethanol, Benzoic Acid, Dehydroacetic Acid, Potassium Sorbate, Farnesol, Iron Oxides (CI 77491, CI 77492, CI 77499).

Other information

- Protect this product from excessive heat and direct sun.

Questions or comments?

Call toll free 866.426.5673

Dist. in USA by
colorescience®
Carlsbad, CA 92011

PRINCIPAL DISPLAY PANEL - 30 mL Bottle Carton

colorescience®

EVEN UP®

CLINICAL PIGMENT
PERFECTOR®

Brightens with Lumira®
ingredient complex

Improves look of discoloration

50
Broad Spectrum
SPF 50
Sunscreen

CHEMICAL-FREE ACTIVES | 100% MINERAL
WATER AND SWEAT RESISTANT, 40 MIN

1 fl. oz. / 30 mL